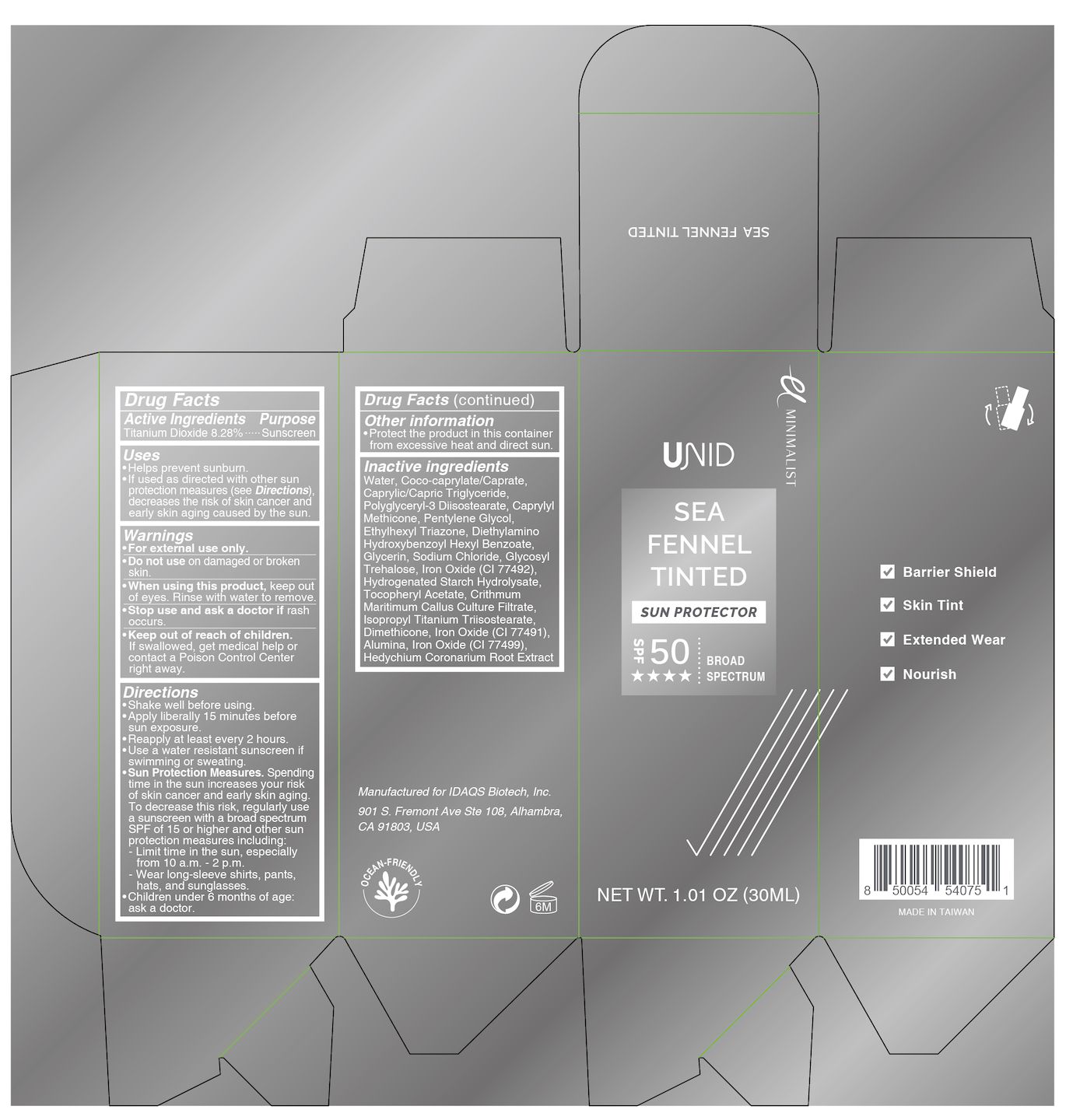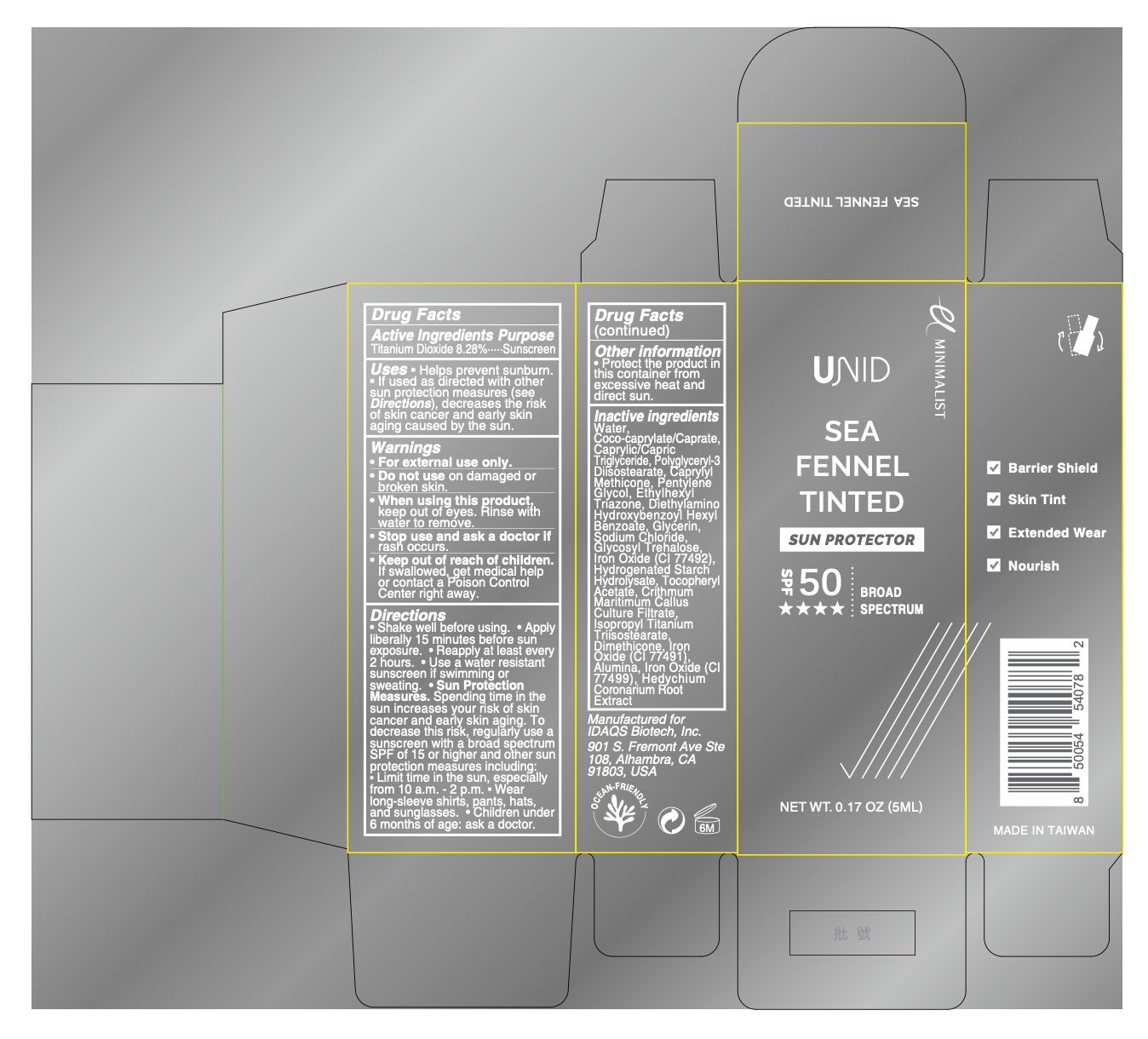 DRUG LABEL: UNID Sea Fennel Tinted Sun Protector
NDC: 83119-245 | Form: CREAM
Manufacturer: Sage Pharmaceuticals Inc
Category: otc | Type: HUMAN OTC DRUG LABEL
Date: 20251223

ACTIVE INGREDIENTS: TITANIUM DIOXIDE 8.28 g/100 g
INACTIVE INGREDIENTS: ALUMINA; CAPRYLYL METHICONE; CRITHMUM MARITIMUM; CAPRYLIC/CAPRIC TRIGLYCERIDE; GLYCERIN; CI 77491; HEDYCHIUM CORONARIUM ROOT; .ALPHA.-TOCOPHEROL ACETATE, DL-; COCO-CAPRYLATE/CAPRATE; ISOPROPYL TITANIUM TRIISOSTEARATE; POLYGLYCERYL-3 DIISOSTEARATE; PENTYLENE GLYCOL; WATER; CI 77499; DIETHYLAMINO HYDROXYBENZOYL HEXYL BENZOATE; GLUCOSYL TREHALOSE; DIMETHICONE; ETHYLHEXYL TRIAZONE; CI 77492; HYDROGENATED STARCH HYDROLYSATE; SODIUM CHLORIDE

UNID Sea Fennel Tinted Sun Protector

Active Ingredients

Titanium Dioxide 8.28%

Purpose

Sunscreen

Uses

- Helps prevent sunburn.
- If used as directed with other sun protection measures (see Directions), decreases the risk of skin cancer and early skin aging caused by the sun.

Warnings

- For external use only.

- Do not use on damaged or broken skin.

- When using this product, keep out of eyes. Rinse with water to remove.

- Stop useand ask a doctor if rash occurs.

- Keep out of reach of children. If swallowed, get medical help or contact a Poison Control Center right away.

Directions

- Shake well before using.
- Apply liberally 15 minutes before sun exposure.
- Reapply at least every 2 hours.
- Use a water resistant sunscreen if swimming or sweating.
- Sun Protection Measures. Spending time in the sun increases your risk of skin cancer and early skin aging. To decrease this risk, regularly use a sunscreen with a broad spectrum SPF of 15 or higher and other sun protection measures including:
  - Limit time in the sun, especially from 10 a.m.–2 p.m.
  - Wear long-sleeve shirts, pants, hats, and sunglasses.
- Children under 6 months of age: ask a doctor.

OTHER SAFETY INFORMATION

- Protect the product in this container from excessive heat and direct sun.

Inactive Ingredients

Water, Coco-caprylate/Caprate, Caprylic/Capric Triglyceride, Polyglyceryl-3 Diisostearate, Caprylyl Methicone, Pentylene Glycol, Ethylhexyl Triazone, Diethylamino Hydroxybenzoyl Hexyl Benzoate, Glycerin, Sodium Chloride, Glycosyl Trehalose, Iron Oxide (CI 77492), Hydrogenated Starch Hydrolysate, Tocopheryl Acetate, Crithmum Maritimum Callus Culture Filtrate, Isopropyl Titanium Triisostearate, Dimethicone, Iron Oxide (CI 77491), Alumina, Iron Oxide (CI 77499), Hedychium Coronarium Root Extract

Sage Pharmaceuticals Inc

Product of Taiwan

Manufactured for IDAQS Biotech, Inc.

Distributed by Beauty River International Inc.
901 S. Fremont Ave 108, Alhambra, CA 91803-4703, USA